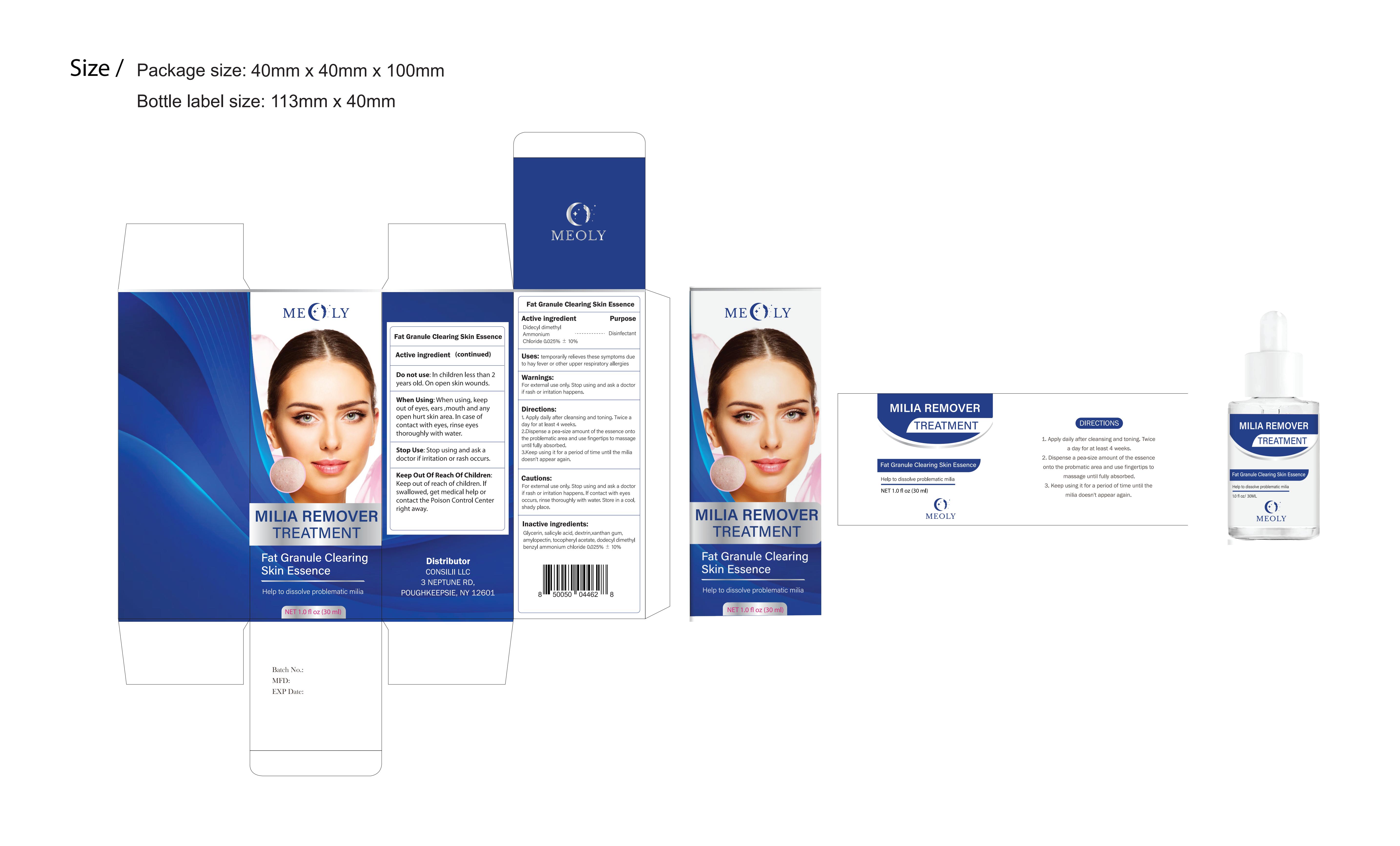 DRUG LABEL: MEOLY Milia Remover 30 ml
NDC: 83818-007 | Form: LIQUID
Manufacturer: Shenzhen Xinxin Yunhai Technology Co., Ltd.
Category: otc | Type: HUMAN OTC DRUG LABEL
Date: 20241125

ACTIVE INGREDIENTS: DIDECYLDIMONIUM CHLORIDE 0.025 g/100 mL
INACTIVE INGREDIENTS: ALPHA-TOCOPHEROL ACETATE; SALICYLIC ACID; AMYLOPECTIN (4,5-DIHYDROXY-1,3-DIMETHYLIMIDAZOLIDIN-2-ONE CROSS LINKED); DODECYLHEXADECYLTRIMONIUM CHLORIDE; XANTHAN GUM; GLYCERIN; DEXTRIN, CORN

83818-007

Active Ingredient

dimethylAmmoniumChloride 0.025%

Purpose

Disinfectant

Use

temporarily relieves these symptoms dueto hay fever or other upper respiratory allergies

Warnings

For external use only, Stop using and ask a doctorif rash or irritation happens.

Do not use

In children less thanyears old. On open skin wounds.

When Using

When using, keepout of eyes,ears ,mouth and anyopen hurt skin area.
In case ofcontact with eyes, rinse eyesthoroughly with water.

Stop Use

Stop using and ask adoctor if irritation or rash occurs.

Ask Doctor

Stop using and ask adoctor if irritation or rash occurs.

Keep Oot Of Reach Of Children

Keep out of reach of children. lfswallowed, get medical help orcontact the Poison Control Centerright away.

Directions

1. Apply daily after cleansing and toning.

Twice aday for at least 4 weeks.2.Dispense a pea-size amount of the essence ontothe problematic area and use fingertips to massageuntil fully absorbed.3.Keep using it for a period of time until the miliadoesn't appear again

Inactive ingredients

Glycerin, salicyle acid, dextrin,xanthan gum,amylopectin, tocopheryl acetate, dodecyl dimethybenzyl ammonium chloride